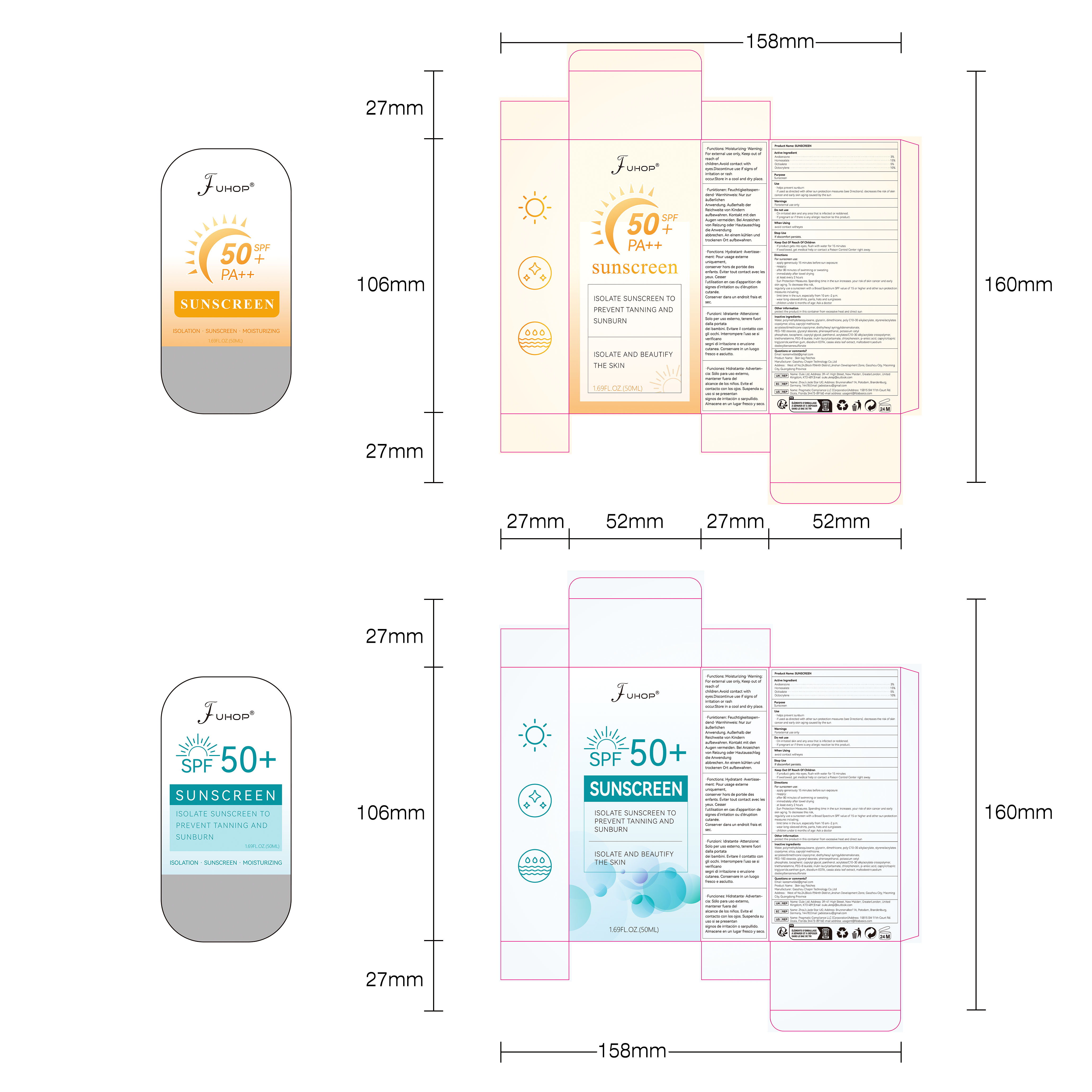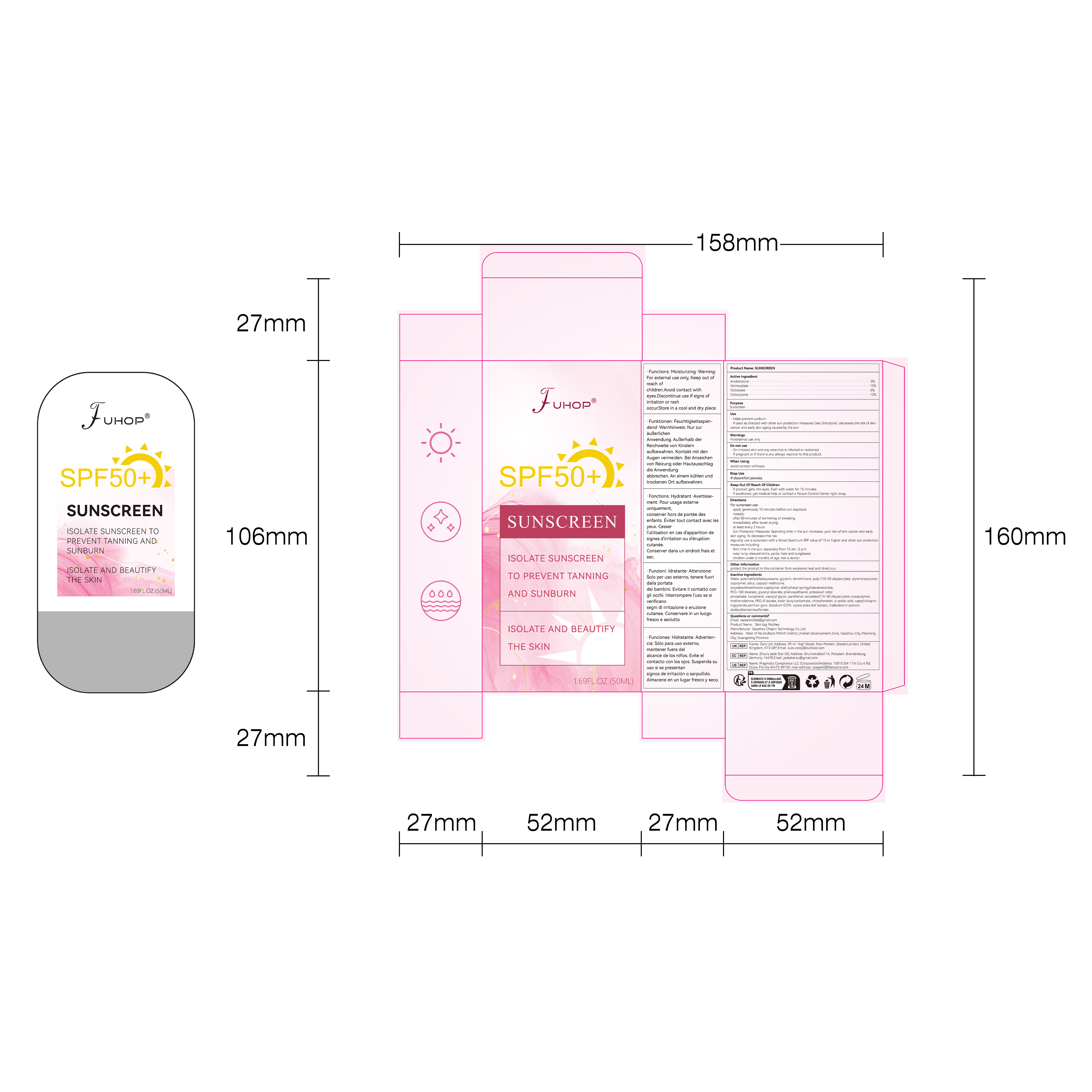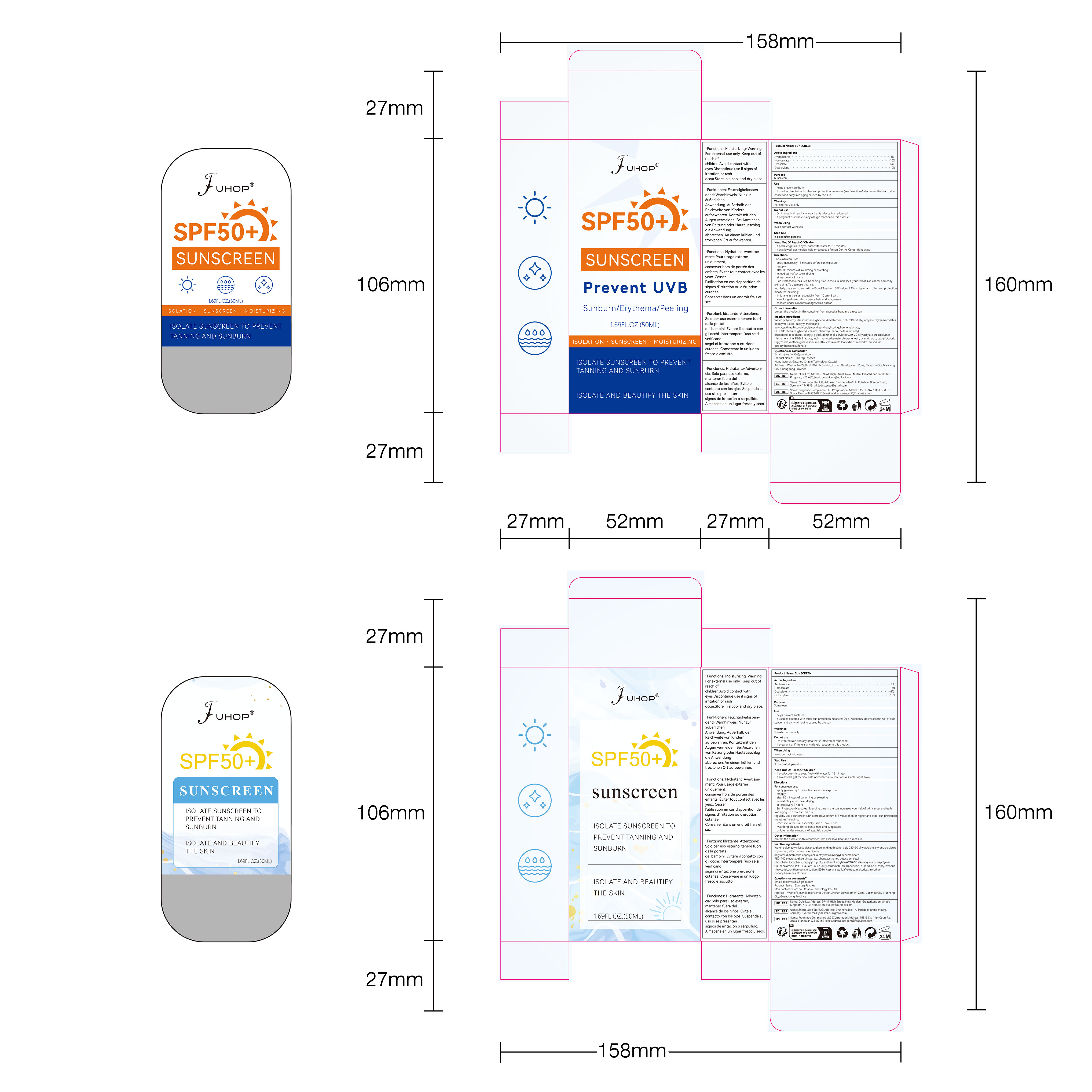 DRUG LABEL: SUNSCREEN
NDC: 84168-050 | Form: CREAM
Manufacturer: Gaozhou Chapin Technology Co., Ltd
Category: otc | Type: HUMAN OTC DRUG LABEL
Date: 20240730

ACTIVE INGREDIENTS: OCTISALATE 5 g/100 mL; HOMOSALATE 15 g/100 mL; OCTOCRYLENE 10 g/100 mL; AVOBENZONE 3 g/100 mL
INACTIVE INGREDIENTS: SENNA ALATA LEAF; ACRYLIC ACID/2-ETHYLHEXYL ACRYLATE/STYRENE COPOLYMER (500000 MW); PEG-8 LAURATE; SODIUM DODECYLBENZENESULFONATE; P-ANISIC ACID; WATER; POLYOXYL 100 STEARATE TYPE I; PANTHENOL; TOCOPHEROL; TROLAMINE; MALTODEXTRIN; SILICON DIOXIDE; CAPRYLYL TRISILOXANE; GLYCERYL MONOSTEARATE; DIETHYLHEXYL SYRINGYLIDENEMALONATE; DIMETHICONE; POLYMETHYLSILSESQUIOXANE (4.5 MICRONS); CAPRYLYL GLYCOL; CHLORPHENESIN; BEHENYL ACRYLATE POLYMER; EDETATE DISODIUM ANHYDROUS; XANTHAN GUM; MEDIUM-CHAIN TRIGLYCERIDES; ACRYLATES/C10-30 ALKYL ACRYLATE CROSSPOLYMER (60000 MPA.S AT 0.5%); POTASSIUM CETYL PHOSPHATE; 2-ETHYLHEXYL ACRYLATE, METHACRYLATE, METHYL METHACRYLATE, OR BUTYL METHACRYLATE/HYDROXYPROPYL DIMETHICONE COPOLYMER (30000-300000 MW); GLYCERIN; INULIN LAURYL CARBAMATE; PHENOXYETHANOL

Active Ingredient

Avobenzone 3%
Homosalate 15%
Octisalate 5%
Octocrylene 10%

Purpose

Sunscreen

Use

● helps prevent sunburn
● if used as directed with other sun protection measures (see Directions). decreases the risk of skin cancer and early skin aging caused by the sun

Warnings

Forexternal use only

Do not use

■On irritated skin and any area that is infected or reddened.
■If pregnant or if there is any allergic reaction to this product.

When Using

avoid contact witheyes

Stop Use

If discomfort persists.

Keep Out Of Reach Of Children

■If product gets into eyes, flush with water for 15 minutes
■If swallowed, get medical help or contact a Poison Control Center right away.

Inactive ingredients

GLYCERYL MONOSTEARATE,2-ETHYLHEXYL ACRYLATE, METHACRYLATE, METHYL METHACRYLATE, OR BUTYL METHACRYLATE/HYDROXYPROPYL DIMETHICONE COPOLYMER (30000-300000 MW),DIETHYLHEXYL SYRINGYLIDENEMALONATE,CAPRYLYL GLYCOL,CHLORPHENESIN,EDETATE DISODIUM ANHYDROUS,BEHENYL ACRYLATE POLYMER,POLYOXYL 100 STEARATE,TOCOPHEROL,TROLAMINE,SENNA ALATA LEAF,GLYCERIN,DIMETHICONE,ACRYLIC ACID/2-ETHYLHEXYL ACRYLATE/STYRENE COPOLYMER (500000 MW) ,ACRYLATES/C10-30 ALKYL ACRYLATE CROSSPOLYMER (60000 MPA.S),XANTHAN GUM,WATER,POTASSIUM CETYL PHOSPHATE ,PANTHENOL ,PEG-8 LAURATE,INULIN LAURYL CARBAMATE,P-ANISIC ACID,MEDIUM-CHAIN TRIGLYCERIDES,MALTODEXTRIN,SODIUM DODECYLBENZENESULFONATE,POLYMETHYLSILSESQUIOXANE (4.5 MICRONS) ,SILICON DIOXIDE,CAPRYLYL TRISILOXANE,PHENOXYETHANOL

DOSAGE & ADMINISTRATION SECTION

Apply according to actual needs each time. Each 100ml contains Avobenzone 3g, Homosalate 15%, Octisalate 5%, Octocrylene 10%